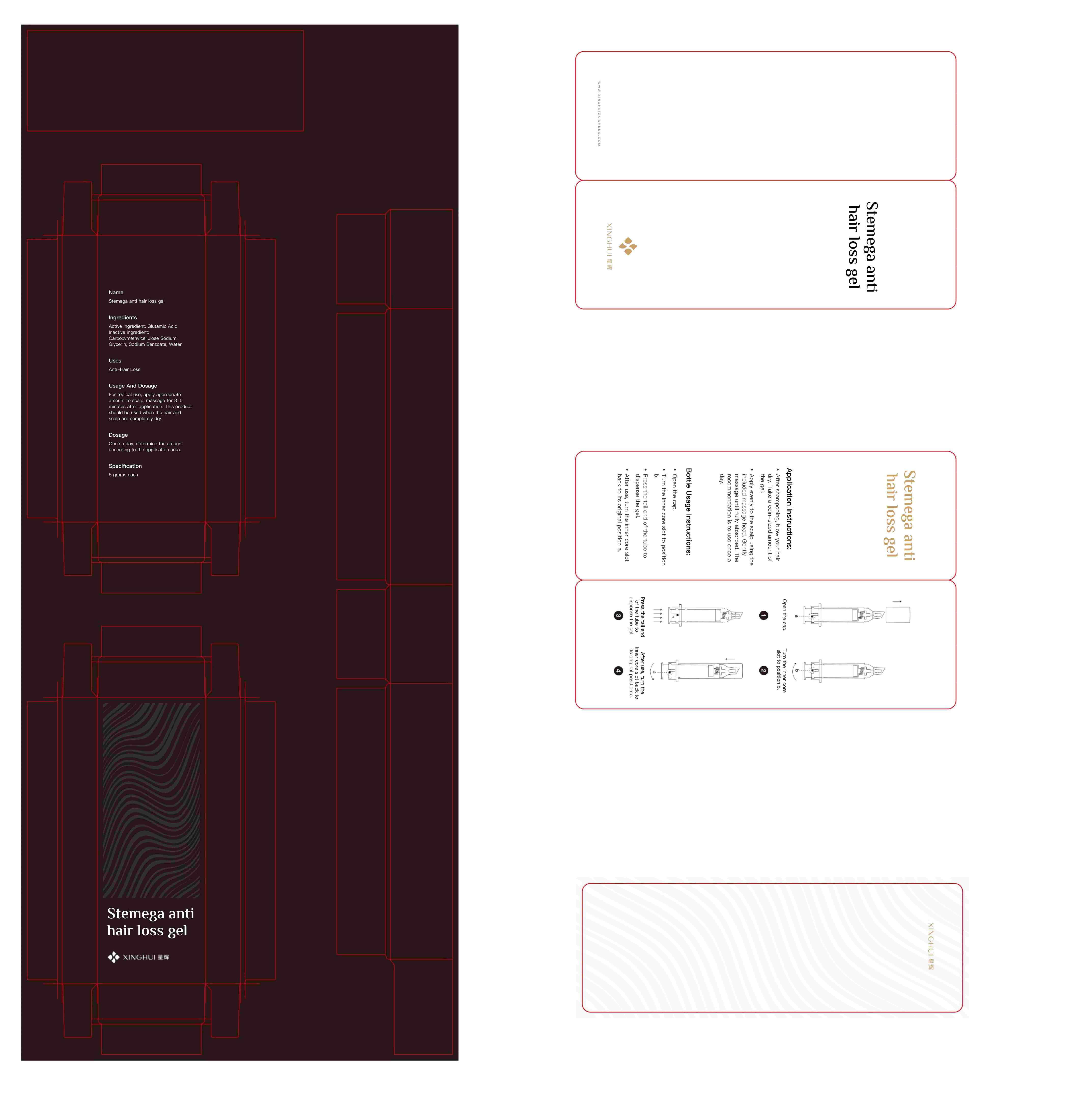 DRUG LABEL: Stemega anti hair loss gel
NDC: 83117-008 | Form: GEL
Manufacturer: Beijing Xinghui Regeneration Technology Co., LTD.
Category: otc | Type: HUMAN OTC DRUG LABEL
Date: 20240627

ACTIVE INGREDIENTS: GLUTAMIC ACID 0.1 g/5 mL
INACTIVE INGREDIENTS: SODIUM BENZOATE 0.025 mL/5 mL; GLYCERIN 0.5 mL/5 mL; CARBOXYMETHYLCELLULOSE SODIUM 0.3 mL/5 mL; WATER 4.075 mL/5 mL

ACTIVE INGREDIENT

Glutamic acid

WARNINGS

1．This product should only be used topically on the scalp and should not be taken orally or applied to other areas of the body.

2．This product may burn and irritate the eyes. In case of contact with sensitive surfaces (eyes, chafed areas, mucous membranes), flush the area with plenty of cold water.

3．If you have any of the following symptoms, please stop taking the medicine and seek medical attention: chest tightness, tachycardia, dizziness, or general weakness; Sudden, unexplained weight gain; Swollen hands and feet; Redness, swelling and allergies.

4．Pregnant women, lactating women and the elderly over 65 years old should use this product with caution. If necessary, it should be guided by a doctor or pharmacist.

5．People allergic to this product should not use it. Use with caution in patients with allergic constitution

6. Do not use this product when the character changes.

7. Keep this product out of reach of children.

8. If you are using other drugs, please consult your doctor or pharmacist before using this product

Keep this product out of reach of children.

PURPOSE

Anti-Hair Loss

STOP USE

If you have any of the following symptoms, please stop taking the medicine and seek medical attention: chest tightness, tachycardia, dizziness, or general weakness; Sudden, unexplained weight gain; Swollen hands and feet; Redness, swelling and allergies.

DOSAGE AND ADMINISTRATION

For topical use, apply appropriate amount to scalp, massage for 3-5 minutes after application. This product should be used when the hair and scalp are completely dry.

Dosage: Once a day, determine the amount according to the application area.

DO NOT USE

1. Pregnant women, lactating women and the elderly over 65 years old should use this product with caution. If necessary, it should be guided by a doctor or pharmacist.

2. People allergic to this product should not use it. Use with caution in patients with allergic constitution

3. Do not use this product when the character changes.

STORAGE AND HANDLING

Store at room temperature, dry and away from light.

INDICATIONS AND USAGE

Anti-Hair Loss

INACTIVE INGREDIENT

Carboxymethylcellulose Sodium; Glycerin; Sodium Benzoate; Water.